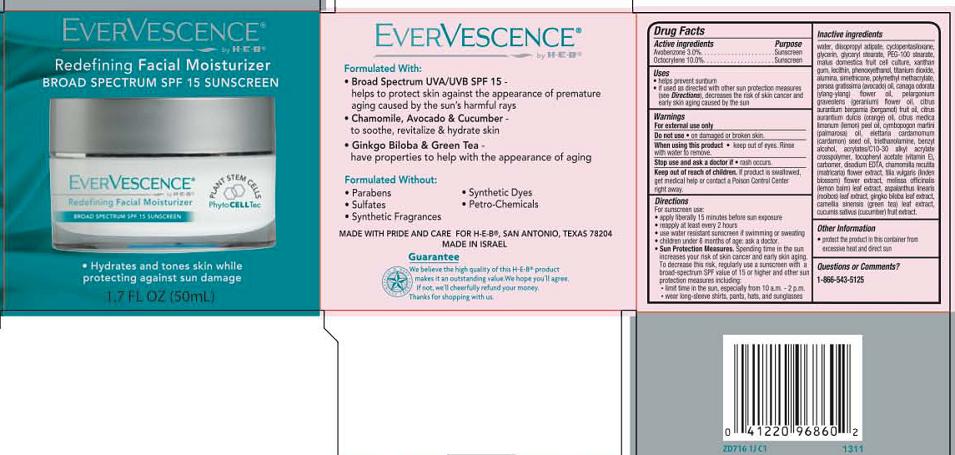 DRUG LABEL: Evervescence Daily Facial Moisturizer Broad Spectrum SPF15 Sunscreen
NDC: 42421-716 | Form: CREAM
Manufacturer: Emilia Personal Care Inc.
Category: otc | Type: HUMAN OTC DRUG LABEL
Date: 20140109

ACTIVE INGREDIENTS: AVOBENZONE 3 g/100 mL; OCTOCRYLENE 10 g/100 mL
INACTIVE INGREDIENTS: WATER; DIISOPROPYL ADIPATE; CYCLOMETHICONE 5; GLYCERIN; GLYCERYL MONOSTEARATE; PEG-100 STEARATE; APPLE; XANTHAN GUM; LECITHIN, SOYBEAN; PHENOXYETHANOL; TITANIUM DIOXIDE; ALUMINUM OXIDE; DIMETHICONE; POLY(METHYL ACRYLATE-CO-METHYL METHACRYLATE-CO-METHACRYLIC ACID 7:3:1; 280000 MW); AVOCADO OIL; CANANGA ODORATA FLOWER; PELARGONIUM GRAVEOLENS FLOWER OIL; BERGAMOT OIL; ORANGE OIL; LEMON OIL; PALMAROSA OIL; CARDAMOM OIL; TROLAMINE; BENZYL ALCOHOL; CARBOMER INTERPOLYMER TYPE A (ALLYL SUCROSE CROSSLINKED); .ALPHA.-TOCOPHEROL ACETATE; EDETATE DISODIUM; CHAMOMILE; TILIA X EUROPAEA FLOWER; MELISSA OFFICINALIS LEAF; ASPALATHUS LINEARIS LEAF; GINKGO; GREEN TEA LEAF; CUCUMBER

EverVescence® Daily Facial Moisturizer
Broad Spectrum SPF15 Sunscreen

Active ingredient

Avobenzone, 3.0%
Octocrylene, 10.0%

Purpose

Sunscreen

Uses

- helps prevent sunburn
- if used as directed with other sun protection measures (see Directions), decreases the risk of skin cancer and early skin aging caused by the sun.

Warnings

For external use only.

Do not use on

damaged or broken skin.

When using this product

- keep out of eyes. Rinse with water to remove.

Stop use and ask a doctor if

- rash occurs.

Keep Out of Reach of Children

If product is swallowed, get medical help or contact a Poison Control Center right away.

Directions

For sunscreen use:
- apply liberally 15 minutes before sun exposure
- reapply at least every 2 hours
- use water resistant sunscreen if swimming or sweating
- children under 6 months: ask a doctor
- Sun Protection Measures: Spending time in the sun increases your risk of skin cancer and early skin aging. To decrease this risk, regularly use a sunscreen with a Broad Spectrum SPF value of 15 or higher and other sun protection measures including:
  - limit time in the sun, especially from 10 a.m. – 2 p.m.
  - wear long-sleeved shirts, pants, hats and sunglasses

Inactive Ingredients

water, diisopropyl asipate, cyclopentasiloxane, glycerin, glyceryl stearate, PEG-100 stearate, malus domestica fruit cell culture, xanthan gum, lecithin, phenoxyethanol, titanium dioxide, alumina, simethicone, polymethyl methacrylate, persea gratissima (avocado) oil, canaga odorata (ylang-ylang) flower oil, pelargonium graveolens (geranium) flower oil, citrus aurantium bergamia (bergamot) fruit oil, citrus aurantium dulcis (orange) oil, citrus medica limonum (lemon) peel oil, cymbopogon martini (palmarosa) oil, elettaria cardamomum (cardamon) seed oil, triethanolamine, benzyl alcohol, acrylates/C10-30 alkyl acrylate crosspolymer, tocopheryl acetate (vitamin E), carbomer, disodium EDTA, chamomilla recutita (matricaria) flower extract, tilia vulgaris (linden blossom) flower extract, melissa officinalis leaf extract, aspalanthus linearis (rooibos) leaf extract, gingko biloba leaf extract, camellia sinensis leaf extract, cucumis sativus (cucumber) fruit extract

Other Information

protect the product in this container from excessive heat and direct sun

Questions or Comments?

1-866-543-5125

Package/Label Principal Display Panel

EverVescence®
Redefining Facial Moisturizer
Broad Spectrum SPF15 Sunscreen

- Hydrates and tones skin while protecting against sun damage

1.7 FL OZ (50mL)

Formulated with:

- Broad Spectrum UVA/UVB SPF 15 – helps to protect skin against the appearance of premature aging caused by the sun’s harmful rays
- Chamomile, Avocado & Cucumber – to soothe, revitalize & hydrate skin
- Ginkgo Biloba & Green Tea – have properties to help with the appearance of aging

Formulated Without:

- Parabens
- Sulfates
- Synthetic Fragrances
- Synthetic Dyes
- Petro-Chemicals

MADE WITH PRIDE AND CARE FOR H-E-B®, SAN ANTONIO, TEXAS 78204

MADE IN ISRAEL

Guarantee

We believe the high quality of this H_E_B® product makes it an outstanding value. We hope you agree. If not, we’ll cheerfully refund your money.
Thanks for shopping with us.

Carton Label